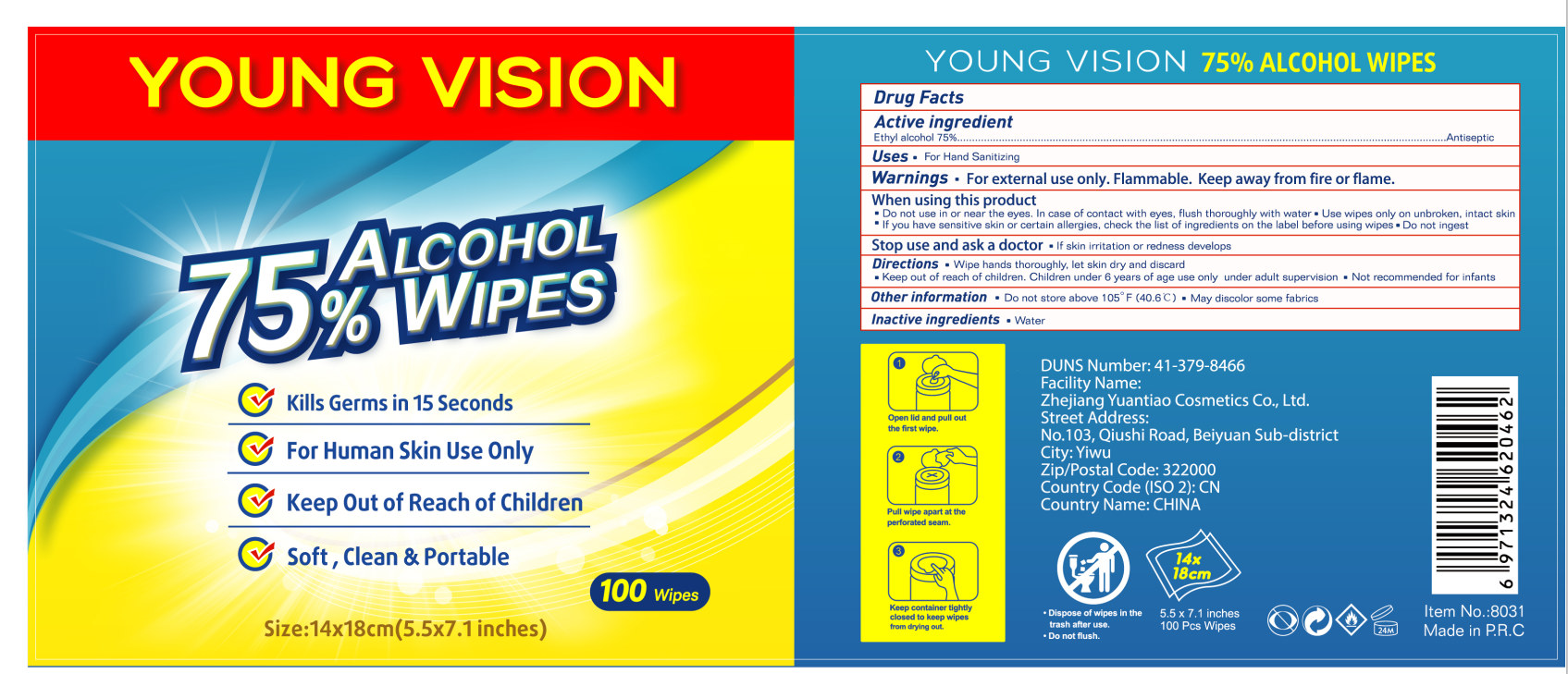 DRUG LABEL: Alcohol Wipes
NDC: 74737-2020 | Form: CLOTH
Manufacturer: Zhejiang Yuantiao Cosmetics Co., Ltd.
Category: otc | Type: HUMAN OTC DRUG LABEL
Date: 20200811

ACTIVE INGREDIENTS: ALCOHOL 166 g/100 1
INACTIVE INGREDIENTS: WATER

DOSAGE AND ADMINISTRATION

Do not store above 105° F (40.6°C)

INACTIVE INGREDIENT

Water

INDICATIONS AND USAGE

Wipe hands thoroughly, let skin dry and discard

ACTIVE INGREDIENT

Ethyl Alcohol

Keep out of reach of children. Children under 6 years of age use only under adult supervision

PURPOSE

Disinfection
Sterilization
No Rinseing

WARNINGS

For external use only. Flammable. Keep away from fire or flame.